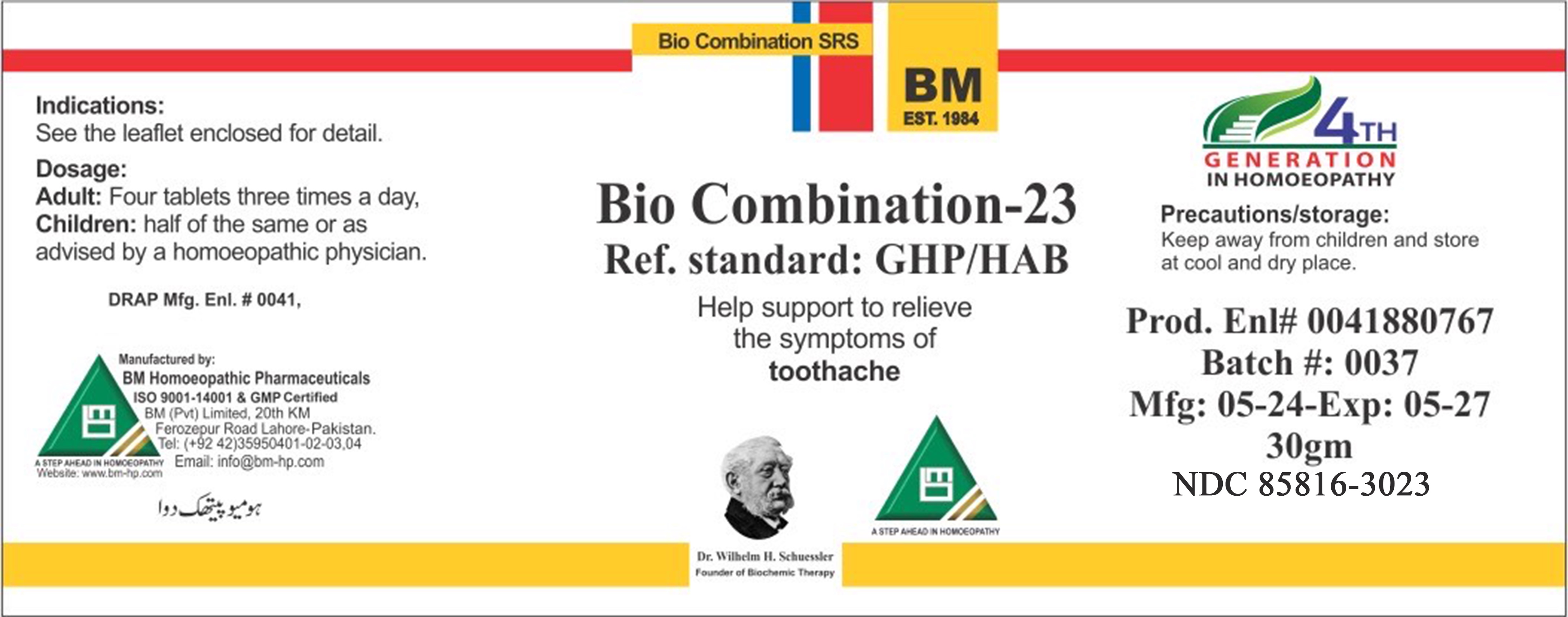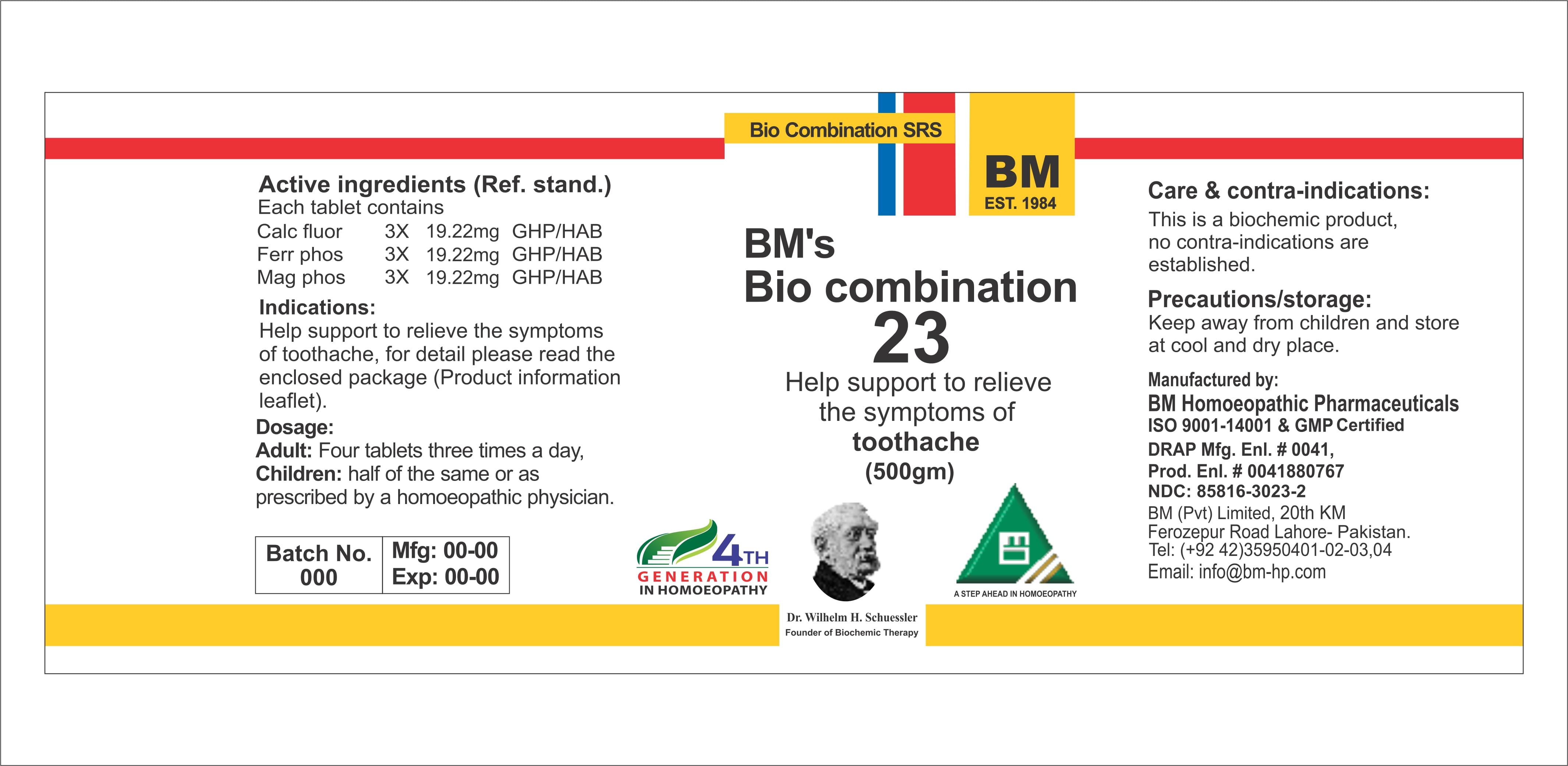 DRUG LABEL: BM HOMEOPATHIC REMEDY BIO COM 23 TOOTHACHE
NDC: 85816-3023 | Form: GLOBULE
Manufacturer: BM Private Limited
Category: homeopathic | Type: HUMAN OTC DRUG LABEL
Date: 20260212

ACTIVE INGREDIENTS: CALCIUM FLUORIDE 6 [hp_X]/1 g; MAGNESIUM PHOSPHATE, DIBASIC TRIHYDRATE 6 [hp_X]/1 g; FERROSOFERRIC PHOSPHATE 6 [hp_X]/1 g
INACTIVE INGREDIENTS: MAGNESIUM STEARATE 0.0208 g/1 g; LACTOSE, UNSPECIFIED FORM 0.978 g/1 g

HOMEOPATHIC REMEDY BIO COM 23 TOOTHACHE/ BIO23

Dosage:
Adults: Four tablets three times a day.
Children: half of the same or as advised by a homeopathic physician.

ACTIVE INGREDIENT

Mag phos, calc fluor, ferr phos

INACTIVE INGREDIENT

LACTOSE, MAGNESIUM STEARATE

INDICATIONS AND USAGE

See the enclosed detail for detail

PURPOSE

For detail, please read the enclosed package (product information leaflet)

KEEP OUT OF REACH OF CHILDREN

Precautions/storage:
Keep away from children and store at cool and dry place.

WARNINGS

Precautions/storage:
Keep away from children and store at cool and dry place.

Package 1:

Package 2: